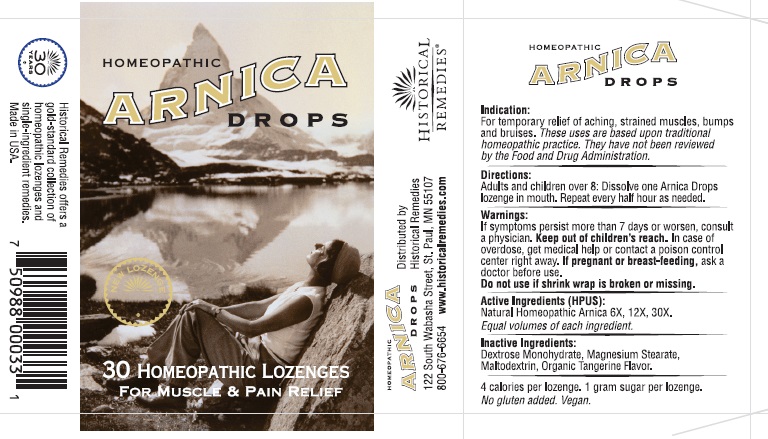 DRUG LABEL: Homeopathic Arnica Drops
NDC: 57556-001 | Form: LOZENGE
Manufacturer: Historical Remedies LLP
Category: otc | Type: HUMAN OTC DRUG LABEL
Date: 20251007

ACTIVE INGREDIENTS: ARNICA MONTANA WHOLE 6 [hp_X]/1 1
INACTIVE INGREDIENTS: DEXTROSE MONOHYDRATE; MAGNESIUM STEARATE; MALTODEXTRIN; LEMON OIL

Active ingredient

Natural Homeopathic Arnica 6X, Arnica 12X, Arnica 30X

Indications

For temporary relief of aching, strained muscles, bumps and bruises. These uses are based upon traditional homeopathic practice. They have not been reviewed by the Food and Drug Administration.

Warning

If symptoms persist more than 7 days or worsen, consult a physician.

Keep out of children’s reach.In case of overdose, get medical help or contact a poison control center right away.

If pregnant or breast-feeding, ask a doctor before use.
Do not use if shrink wrap is broken or missing.

Directions

Adults & children over 8: dissolve one lozenge in mouth. Repeat every half hour as needed.

Inactive Ingredients:

Dextrose Monohydrate, Magnesium Stearate, Maltodextrin, tangerine flavor.

4 calories per lozenge. 1 gram sugar per lozenge.
No gluten added. Vegan.